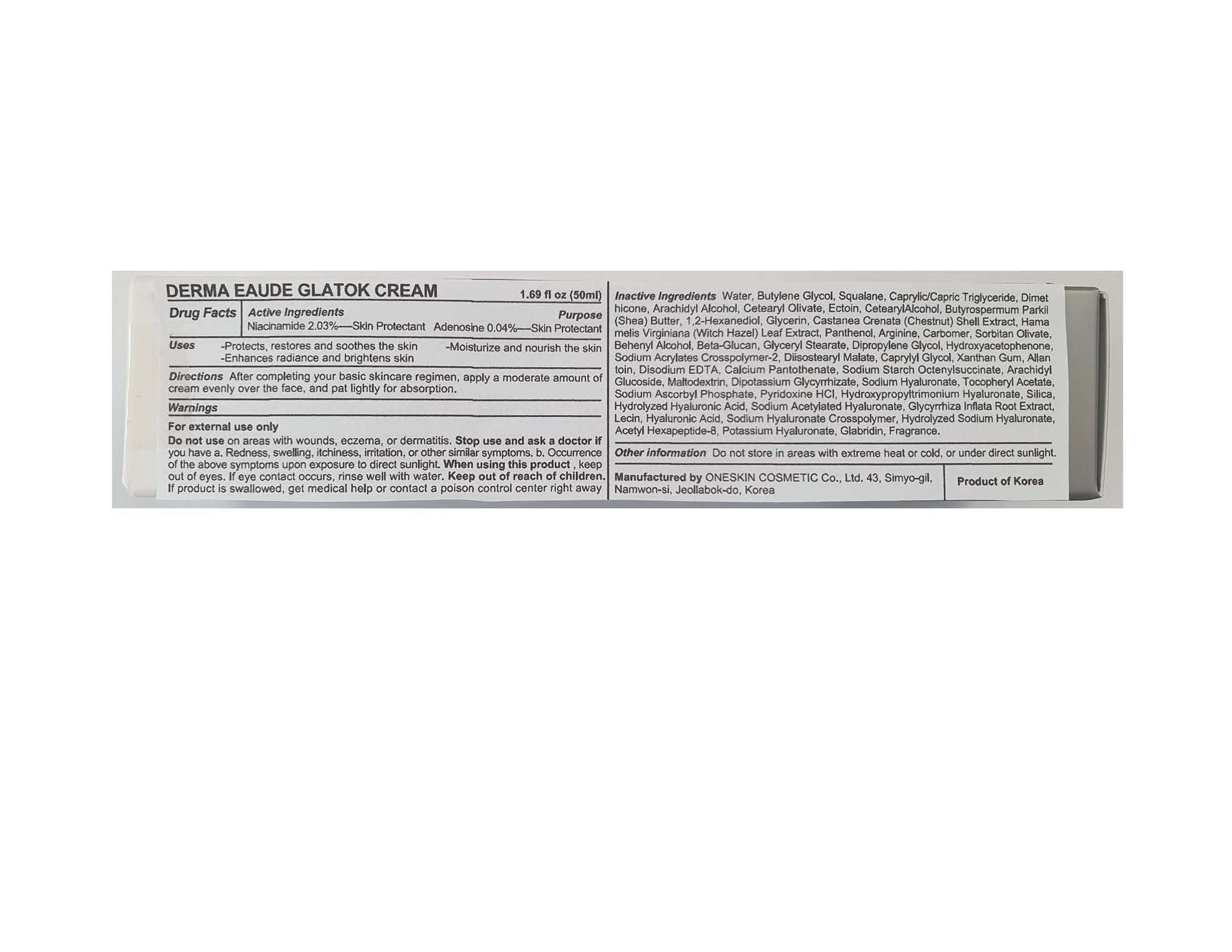 DRUG LABEL: Derma Eaude Glatok Cream
NDC: 70889-910 | Form: CREAM
Manufacturer: Oneskin Cosmetics Co., Ltd.
Category: otc | Type: HUMAN OTC DRUG LABEL
Date: 20201204

ACTIVE INGREDIENTS: ADENOSINE 1.015 g/50 mL; NIACINAMIDE 0.02 g/50 mL
INACTIVE INGREDIENTS: WATER; BUTYLENE GLYCOL; GLYCERIN; ARGININE; ALLANTOIN; EDETATE DISODIUM; HYALURONATE SODIUM; BUTYROSPERMUM PARKII (SHEA) BUTTER UNSAPONIFIABLES; CASTANEA CRENATA SHELL

ACTIVE INGREDIENT

Niacinamide 2.03%

Adenosine 0.04%

PURPOSE

Skin Protectant

INDICATIONS AND USAGE

- Protects, restores and soothes the skin
- Moisturize and nourish the skin
- Enhances radiance and brightens skin

DOSAGE AND ADMINISTRATION

After completing your basic skincare regimen, apply a moderate amount of cream evenly over the face, and pat lightly for absorption.

WARNINGS

For external use only

- Do not use on areas with wounds, eczema, or dermatitis.
- Stop use and ask a doctor if you have

a. Redness, swelling, itchiness, irritation, or other similar symptoms.
b. Occurrence of the above symptoms upon exposure to direct sunlight.

- When using this product, keep out of eyes. If eye contact occurs, rinse well with water.
- Keep out of reach of children. If product is swallowed, get medical help or contact a poison control center right away

Keep out of reach of children. If product is swallowed, get medical help or contact a poison control center right away

INACTIVE INGREDIENT

Water, Butylene Glycol, Squalane, Caprylic/Capric Triglyceride, Dimethicone, Arachidyl Alcohol, Cetearyl Olivate, Ectoin, Cetearyl Alcohol, Butyrospermum Parkii (Shea) Butter, 1,2-Hexanediol, Glycerin, Castanea Crenata (Chestnut) Shell Extract, Hamamelis Virginiana (Witch Hazel) Leaf Extract, Panthenol, Arginine, Carbomer, Sorbitan Olivate, Behenyl Alcohol, Beta-Glucan, Glyceryl Stearate, Dipropylene Glycol, Hydroxyacetophenone, Sodium Acrylates Crosspolymer-2, Diisostearyl Malate, Caprylyl Glycol, Xanthan Gum, Allantoin, Disodium EDTA, Calcium Pantothenate, Sodium Starch Octenylsuccinate, Arachidyl Glucoside, Maltodextrin, Dipotassium Glycyrrhizate, Sodium Hyaluronate, Tocopheryl Acetate, Sodium Ascorbyl Phosphate, Pyridoxine HCl, Hydroxypropyltrimonium Hyaluronate, Silica, Hydrolyzed Hyaluronic Acid, Sodium Acetylated Hyaluronate, Glycyrrhiza Inflata Root Extract, Lecithin, Hyaluronic Acid, Sodium Hyaluronate Crosspolymer, Hydrolyzed Sodium Hyaluronate, Acetyl Hexapeptide-8, Potassium Hyaluronate, Glabridin, Fragrance.

OTHER SAFETY INFORMATION

- Do not store in areas with extreme heat or cold, or under direct sunlight.